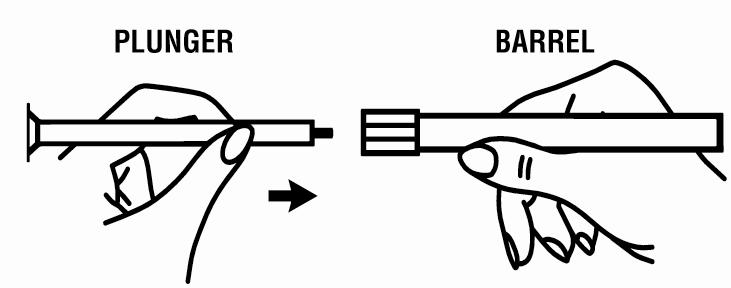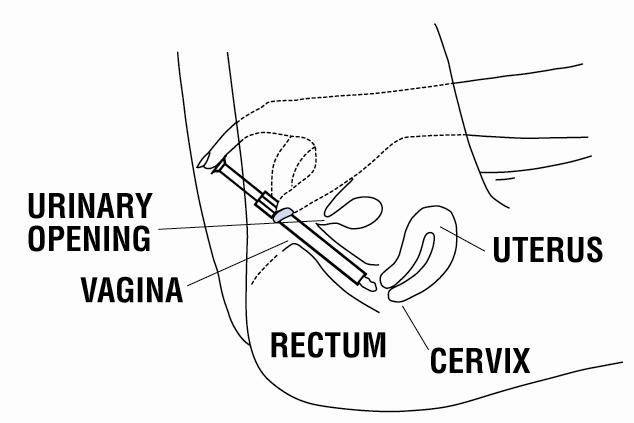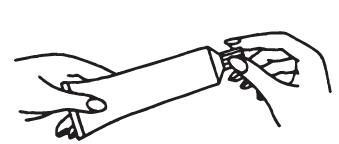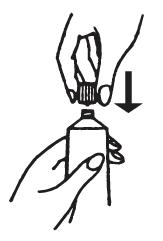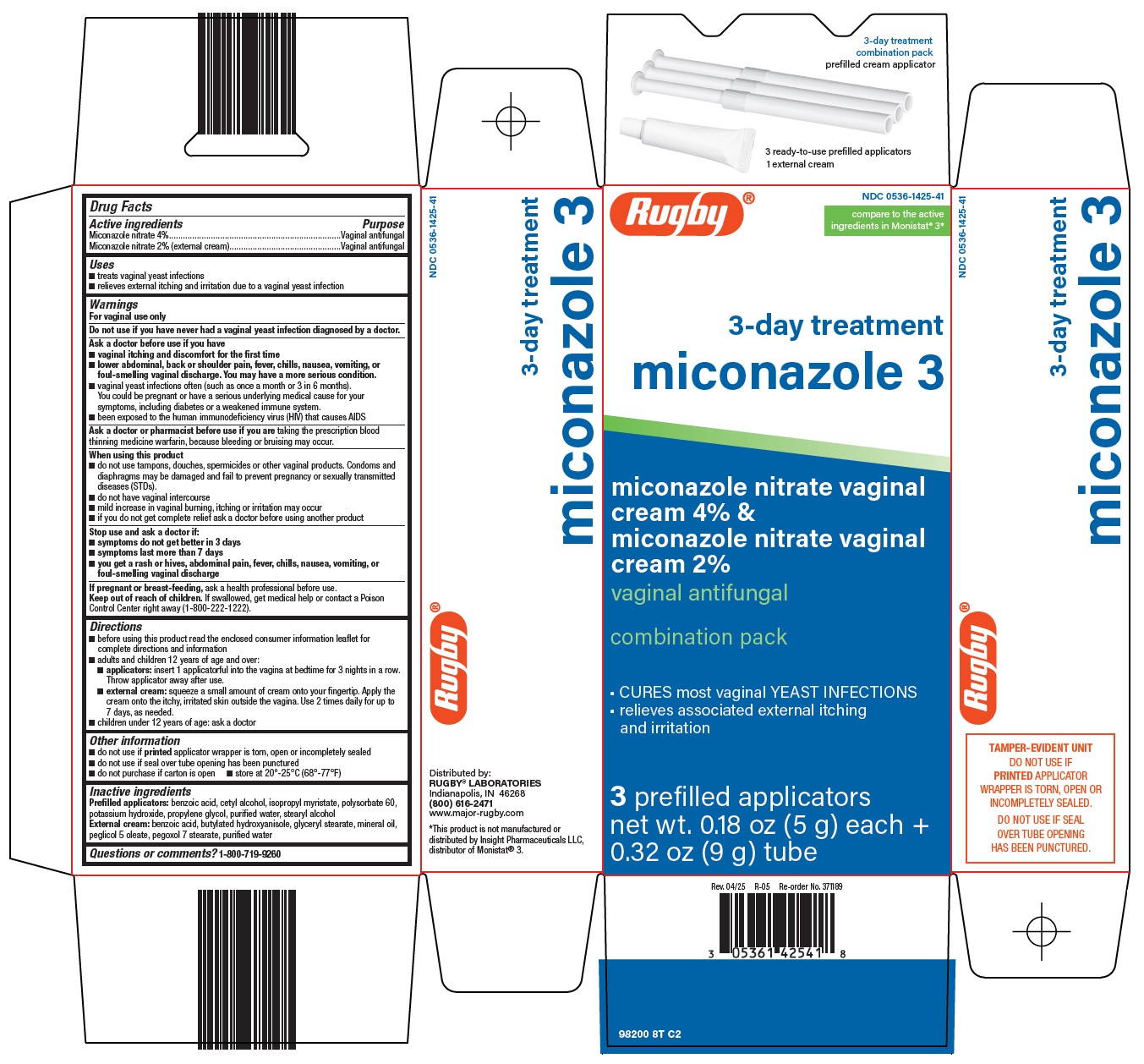 DRUG LABEL: Rugby Miconazole 3
NDC: 0536-1425 | Form: KIT | Route: VAGINAL
Manufacturer: Rugby Laboratories
Category: otc | Type: HUMAN OTC DRUG LABEL
Date: 20260225

ACTIVE INGREDIENTS: MICONAZOLE NITRATE 4 g/100 g; MICONAZOLE NITRATE 2 g/100 g
INACTIVE INGREDIENTS: BENZOIC ACID; CETYL ALCOHOL; ISOPROPYL MYRISTATE; POLYSORBATE 60; POTASSIUM HYDROXIDE; PROPYLENE GLYCOL; WATER; STEARYL ALCOHOL; BENZOIC ACID; BUTYLATED HYDROXYANISOLE; GLYCERYL MONOSTEARATE; MINERAL OIL; WATER; PEG-5 OLEATE; PEGOXOL 7 STEARATE

Rugby Laboratories Miconazole 3 Drug Facts

Active ingredients

Miconazole nitrate 4%

Miconazole nitrate 2% (external cream)

Purpose

Vaginal antifungal

Uses

- treats vaginal yeast infections
- relieves external itching and irritation due to a vaginal yeast infection

Warnings

For vaginal use only

Do not use

if you have never had a vaginal yeast infection diagnosed by a doctor.

Ask a doctor before use if you have

- vaginal itching and discomfort for the first time
- lower abdominal, back or shoulder pain, fever, chills, nausea, vomiting, or foul-smelling vaginal discharge. You may have a more serious condition.
- vaginal yeast infections often (such as once a month or 3 in 6 months). You could be pregnant or have a serious underlying medical cause for your symptoms, including diabetes or a weakened immune system.
- been exposed to the human immunodeficiency virus (HIV) that causes AIDS

Ask a doctor or pharmacist before use if you are

taking the prescription blood thinning medicine warfarin, because bleeding or bruising may occur.

When using this product

- do not use tampons, douches, spermicides or other vaginal products. Condoms and diaphragms may be damaged and fail to prevent pregnancy or sexually transmitted diseases (STDs).
- do not have vaginal intercourse
- mild increase in vaginal burning, itching or irritation may occur
- if you do not get complete relief ask a doctor before using another product

Stop use and ask a doctor if

- symptoms do not get better in 3 days
- symptoms last more than 7 days
- you get a rash or hives, abdominal pain, fever, chills, nausea, vomiting, or foul-smelling vaginal discharge

If pregnant or breast-feeding,

ask a health professional before use.

Keep out of reach of children.

If swallowed, get medical help or contact a Poison Control Center right away (1-800-222-1222).

Directions

- before using this product read the enclosed consumer information leaflet for complete directions and information
- adults and children 12 years of age and over:
  - applicators: insert 1 applicatorful into the vagina at bedtime for 3 nights in a row. Throw applicator away after use.
  - external cream: squeeze a small amount of cream onto your fingertip. Apply the cream onto the itchy, irritated skin outside the vagina. Use 2 times daily for up to 7 days, as needed.
- children under 12 years of age: ask a doctor

Other information

- do not use if printed applicator wrapper is torn, open or incompletely sealed
- do not use if seal over tube opening has been punctured
- do not purchase if carton is open
- store at 20°-25°C (68°-77°F)

Inactive ingredients

Prefilled applicators: benzoic acid, cetyl alcohol, isopropyl myristate, polysorbate 60, potassium hydroxide, propylene glycol, purified water, stearyl alcohol

External cream: benzoic acid, butylated hydroxyanisole, glyceryl stearate, mineral oil, peglicol 5 oleate, pegoxol 7 stearate, purified water

Questions or comments?

1-800-719-9260

Consumer Information

3-Day Treatment

CONSUMER INFORMATION LEAFLET

Miconazole Nitrate Vaginal Cream (4%) and Miconazole Nitrate Cream (2%)

VAGINAL ANTIFUNGAL

COMBINATION PACK

Cures Most Vaginal Yeast Infections and Relieves Associated External Itching and Irritation

Why should I use this product?

This product contains 3 cream prefilled applicators that cure most vaginal yeast infections, plus an external cream that can be used for relief of itching and irritation on the skin outside the vagina (vulva) due to a yeast infection. Do not use this product if this is the first time you have vaginal discharge, itching, burning and discomfort. See your doctor or health professional first to find out the cause of your symptoms. If a doctor has told you in the past that you had a vaginal yeast infection and you have the same symptoms now (such as vaginal discharge, itching or burning), then this product may work for you.

What is a vaginal yeast infection?

A vaginal yeast infection is a common condition caused by an overgrowth of yeast (Candida) that may normally live in the vagina. Your doctor may call this infection "monilia" or "candidiasis." Some women may have a yeast infection on the skin outside of the vagina (vulva) at the same time that they have a vaginal infection.

Who can get a vaginal yeast infection?

You can get a vaginal yeast infection at any age. It is most common during the childbearing years. Women who are pregnant or diabetic, taking antibiotics, birth control pills or steroids, or who have a weakened immune system are more likely to get repeated yeast infections that may not clear up easily with proper treatment.

Some medical conditions can weaken the body's normal ability to fight infection. One of the most serious of these conditions is infection with the human immunodeficiency virus (HIV - the virus that causes AIDS). The HIV virus causes the body to be more likely to get infections, including vaginal yeast infections that may not clear up easily with proper treatment. If you may have been exposed to HIV and get repeated vaginal yeast infections, you should see your doctor right away. For more information on HIV infection, please contact your doctor or the CDC National AIDS HOTLINE. The CDC phone numbers are:

1-800-232-4636 (English/Spanish), or 1-888-232-6348 (hearing impaired, TTY).

How can I tell if I have a vaginal yeast infection?

When you have a vaginal yeast infection, you may have one or more of the following symptoms:

- vaginal itching
- vaginal discharge that may be thick, white, and lumpy like cottage cheese
- vaginal soreness, irritation, or burning
- rash or redness on the skin outside the vagina (vulva)
- burning on urination
- painful vaginal intercourse (sex)

Note: Vaginal yeast infections do NOT cause fever, chills, lower abdominal, back or shoulder pain, foul-smelling vaginal discharge, or a missed period. These may be signs of a sexually transmitted disease (STD) or a tubal pregnancy. If you have these symptoms, call your doctor right away.

What are other causes of a vaginal discharge?

It is normal to have a small amount of vaginal discharge at certain times of the month. This normal discharge may be clear or slightly white and does not cause itching, pain or a foul odor.

The most common cause of an abnormal vaginal discharge is an infection. These infections include bacterial vaginosis (BV), trichomoniasis (Trich), gonorrhea (GC) and/or chlamydia. All of these may be transmitted sexually and are called sexually transmitted diseases (STDs). If you have more questions about sexually transmitted diseases (STDs) call the CDC Hotline at 1-800-232-4636.

Although many of the infections mentioned above can cause symptoms similar to a vaginal yeast infection (vaginal discharge, irritation and itching), their diagnosis must be made by a doctor so that proper treatment can be given.

If these infections are not properly treated or if proper treatment is delayed, serious problems, such as pelvic inflammatory disease (PID) may result, which may prevent you from having children in the future. If you are pregnant and do not get the proper treatment, the infection may be passed to your baby before or during delivery and may cause your baby to have permanent damage. If you have multiple sex partners or a new sex partner, you should also ask a doctor before use to make sure you do not have an STD.

Why do women get repeated vaginal yeast infections?

Women may get repeated vaginal yeast infections that may not clear up easily with proper treatment. Listed below are some of the causes of repeated yeast infections:

- hormonal changes occurring a few days before the monthly period
- use of antibiotics
- use of some birth control pills
- pregnancy
- diabetes ("sugar" or "high blood sugar")
- clothing - wearing tight layers or moist clothing in the genital area
- weakened immune system - some drugs (such as chemotherapy or steroids) and medical conditions can weaken the body's normal ability to fight infection. One of the most serious of these conditions is infection with the human immunodeficiency virus (HIV - the virus that causes AIDS). Infection with HIV causes the person to be more likely to get infections, including vaginal yeast infections.

If you get vaginal yeast infections often (such as once a month or 3 in 6 months), you should talk to a doctor.

Are vaginal yeast infections sexually transmitted?

Vaginal yeast infections are usually not spread by having intercourse (sex). However, if your partner has a rash, itching or discomfort in his genital area, he should contact a doctor to find out the cause of his symptoms and tell the doctor that you are treating your vaginal yeast infection with this product.

How can I prevent repeated vaginal yeast infections?

To lower your chances of getting another yeast infection:

• Try to keep the genital area cool and dry. Yeast grow well in warm, moist areas. The following suggestions may be helpful:

(1) Wear cotton underwear and loose-fitting clothes.

(2) Change out of damp clothes or a wet bathing suit as soon as possible.

(3) If you use minipads when you are not having a menstrual period, change the minipads often.

• Talk with your doctor about any drugs you are now taking. You are more likely to get a vaginal yeast infection if you are taking certain drugs such as antibiotics, steroids, or birth control pills. Do not stop taking these drugs without first asking your doctor. A doctor may need to see you to make sure that you do not have other medical conditions such as diabetes or a weakened immune system.

Can I use this product during my menstrual period?

Yes, this product can be used during your menstrual period. In fact, many women get vaginal yeast infections just before their period because of hormonal changes. Using this product during your period will not affect how well this product works. If you have started treatment and your period occurs, you should complete the full course of treatment.

Do not use tampons while using this product, because tampons may remove some of the drug from the vagina. Use deodorant-free sanitary napkins or pads instead, and change them often.

Can I use other vaginal products with this product?

This drug should not be used with other vaginal products.

- Douches and tampons may remove some of the cream from the vagina.
- Spermicides may interfere with this product.
- Condoms and diaphragms may be damaged by this product and fail to prevent pregnancy or sexually transmitted diseases (STDs).

How can I get the best results when treating my infection?

- Use 1 cream prefilled applicator at bedtime, even during your menstrual period for 3 nights in a row.
- Use the tube of cream externally only while symptoms are present. If you have symptoms (such as itching and irritation) on the skin outside the vagina (vulva), apply the cream externally 2 times a day, up to a total of 7 days, as needed.
- Dry the genital area thoroughly after a shower, bath or swim. Change out of a wet bathing suit or damp clothes as soon as possible. A dry area is less likely to lead to the overgrowth of yeast.
- Wear cotton underwear and loose-fitting clothes.
- Wipe from front to back after a bowel movement or after urination.
- Do not douche, because douching may wash the drug out of the vagina.
- Do not use tampons, because they remove some of the drug from the vagina. Use deodorant-free sanitary napkins or pads as needed.
- Do not use spermicides, as they may interfere with this product.
- Do not have vaginal intercourse while using this product.
- Do not scratch the skin outside the vagina. Scratching can cause more irritation and can spread the infection.
- Tell your doctor about any drugs you are now taking. Certain drugs such as antibiotics, steroids, and birth control pills, may make it more likely for you to get a vaginal yeast infection. If you are taking any of these drugs do not stop taking them without first asking a doctor.
- If you have any other medical questions or concerns about vaginal yeast infections, call your doctor.

What warnings should I know about when using this product?

For vaginal use only.

Do not use if you have never had a vaginal yeast infection diagnosed by a doctor.

Ask a doctor before use if you have:

- vaginal itching and discomfort for the first time. You may need a different treatment.
- lower abdominal, back or shoulder pain, fever, chills, nausea, vomiting, or foul-smelling vaginal discharge. You could have a more serious condition.
- vaginal yeast infections often (such as once a month or 3 in 6 months). You could be pregnant or have a serious underlying medical cause for your symptoms, including diabetes or a weakened immune system.
- been exposed to the human immunodeficiency virus (HIV) that causes AIDS.

Ask a doctor or pharmacist before use if you are

taking the prescription blood thinning medicine, warfarin (coumadin), because bleeding or bruising may occur.

When using this product:

- do not use tampons, douches, spermicides, or other vaginal products. Condoms and diaphragms may be damaged and fail to prevent pregnancy or sexually transmitted diseases (STDs).
- do not have vaginal intercourse
- mild increase in vaginal burning, itching or irritation may occur
- if you do not get complete relief ask a doctor before using another product

How Should I Use This Product?

This product is for adults and children 12 years of age and over. For children under 12 years, ask a doctor.

Directions for using the Applicator containing the Vaginal Cream:

Begin treatment before going to bed:

1 Remove the prefilled applicator from the wrapper.

2 Unscrew and remove cap from prefilled applicator.

3 Insert plunger into prefilled applicator by placing small end of plunger into the ribbed end of the applicator.

4 Gently insert the applicator into the vagina as far as it will go comfortably. This can be done while lying on your back with your knees bent (as shown in the picture) or while standing with your feet apart and your knees bent.

5 With one hand holding the barrel, use the other hand to push the plunger all the way in to place the cream as far back in the vagina as possible. Then remove both parts of the applicator from the vagina.

6 Throw the applicator away after use. Do not flush in toilet.

7 Lie down as soon as possible after inserting the cream. This will reduce leakage.

8 Repeat steps 1 through 7 before going to bed for the next 2 days.

You may want to use deodorant-free pads or pantyshields to protect your clothing during the time that you are using this product. This is because the cream can leak or you may get some discharge. Do not use tampons, douches, spermicides, condoms or diaphragms until after you have completed treatment and your symptoms are gone.

Directions for using the External Vulvar Cream

Use the cream twice daily, for up to 7 days as needed.

1. Open the tube by unscrewing the cap. The first time the tube is opened, press the sharp point of the cap into the sealed end of the tube. Push down firmly until the seal is open.

2. Squeeze a small amount of cream onto your fingertip.

3. Apply the cream onto the skin outside the vagina (vulva) that itches and is irritated.

4. Screw the cap back on the tube.

5. Repeat steps 2-4 each morning and at bedtime for up to 7 days, as needed.

Stop use and ask your doctor if:

- symptoms do not get better in 3 days
- symptoms last more than 7 days
- you get a rash or hives, abdominal pain, fever, chills, nausea, vomiting, or foul-smelling vaginal discharge.

These may be signs that this product is not working, or you may have a more serious condition or an allergic reaction.

If pregnant or breast-feeding, ask a health professional before use.

Keep out of reach of children. If swallowed, get medical help or contact a Poison Control Center right away (1-800-222-1222).

What side effects may occur with this product?

A mild increase in vaginal burning, itching, or irritation may occur when the applicator containing the cream is inserted. Abdominal cramping has also been reported.

Stop using this product and consult your doctor if you have abdominal pain, hives, skin rash, or if you have severe vaginal burning, itching, or irritation or swelling.

What should I do if I have questions about this product?

If you have questions of a medical nature, please contact your pharmacist, doctor or health care professional. If you have any other questions or need more information on this product, call our toll-free number 1-800-719-9260.

Other Information:

- TAMPER-EVIDENT UNIT – do not use if printed applicator wrapper is torn, open or incompletely sealed.
- do not use if tube seal has been punctured.
- store at 20°-25°C (68°-77°F)

Active Ingredients: Prefilled Applicators: miconazole nitrate 4% (200 mg per applicator) External Vulvar Cream: miconazole nitrate 2%

Inactive Ingredients: Prefilled Applicators: benzoic acid, cetyl alcohol, isopropyl myristate, polysorbate 60, potassium hydroxide, propylene glycol, purified water, stearyl alcohol. External Vulvar Cream: benzoic acid, butylated hydroxyanisole, glyceryl stearate, mineral oil, peglicol 5 oleate, pegoxol 7 stearate, purified water.

Distributed By

Perrigo®

Allegan, MI 49010

05/20

: 98200 00 J5

Principal Display Panel

Rugby®

compare to the active ingredients in Monistat® 3

3-day treatment

miconazole 3

miconazole nitrate vaginal cream 4% & miconazole nitrate vaginal cream 2%

vaginal antifungal

combination pack

• CURES most vaginal YEAST INFECTIONS

• relieves associated external itching and irritation

3 prefilled applicators

net wt. 0.18 oz (5 g) each + 0.32 oz (9 g) tube